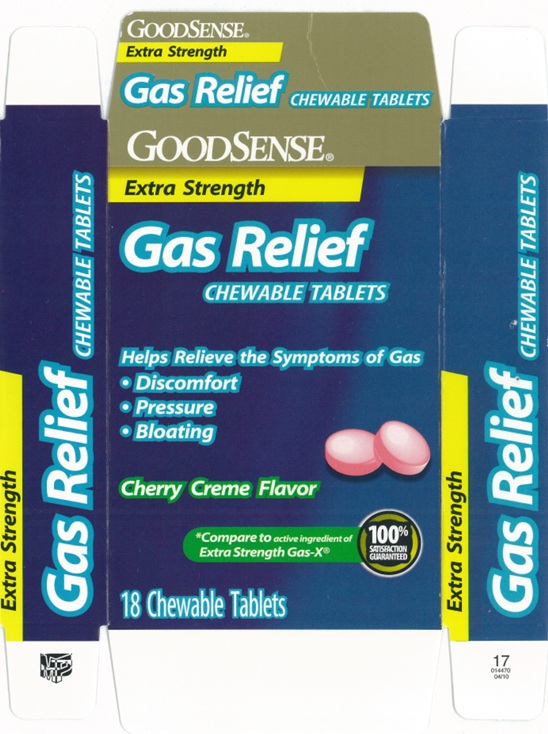 DRUG LABEL: Extra Strength Gas Relief Cherry
NDC: 50804-134 | Form: TABLET, CHEWABLE
Manufacturer: Good Sense (Geiss, Destin & Dunn, Inc.)
Category: otc | Type: Human OTC Drug Label
Date: 20250228

ACTIVE INGREDIENTS: DIMETHICONE 125 mg/1 1
INACTIVE INGREDIENTS: D&C RED NO. 30 ALUMINUM LAKE; MAGNESIUM STEARATE; CELLULOSE, MICROCRYSTALLINE; SORBITOL; SUCROSE; MALTODEXTRIN; DEXTROSE, UNSPECIFIED FORM

Extra Strength Gas Relief Cherry

ACTIVE INGREDIENT(in each tablet)

Simethicone 125 mg

PURPOSE

Anti-gas

USE(S)

relieves:

- pressure
- bloating
- symptoms referred to as gas

WARNINGS

.

KEEP OUT OF REACH OF CHILDREN

In case of overdose, get medical help or contact a Poison Control Center immediately.

DIRECTIONS

- chew 1 to 2 tablets thoroughly as needed after meals and at bedtime
- do not exceed 4 tablets in a 24 hour period except under the advice and supervision of a physician.

OTHER INFORMATION

- do not use if any individual blister unit is broken or open
- store at room temperature
- avoid high humidity and excessive heat, above 40ºC (104ºF)

INACTIVE INGREDIENTS

D&C red # 30 aluminum lake, dextrose, flavor, magnesium stearate, maltodextrin, microcrystalline cellulose, sorbitol, sucrose.

PRINCIPAL DISPLAY PANEL

GOODSENSE

Extra Strength

Gas Relief

CHEWABLE TABLETS

Helps Relieve the Symptoms of Gas:

- Discomfort
- Pressure
- Bloating

Cherry Creme Flavor

*Compare to active ingredient of Extra Strength Gas-X®

18 chewable tablets